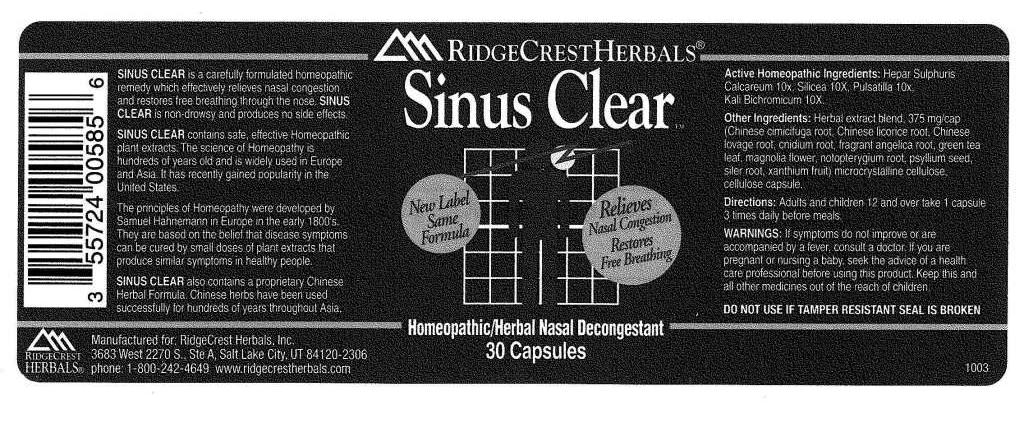 DRUG LABEL: Sinus Clear
NDC: 57520-0133 | Form: CAPSULE
Manufacturer: Apotheca Company
Category: homeopathic | Type: HUMAN OTC DRUG LABEL
Date: 20110225

ACTIVE INGREDIENTS: CALCIUM SULFIDE 10 [hp_X]/1 1; POTASSIUM DICHROMATE 10 [hp_X]/1 1; PULSATILLA VULGARIS 10 [hp_X]/1 1; SILICON DIOXIDE 10 [hp_X]/1 1
INACTIVE INGREDIENTS: ACTAEA CIMICIFUGA ROOT; LICORICE; CNIDIUM ROOT; ANGELICA DAHURICA ROOT; GREEN TEA LEAF; MAGNOLIA GRANDIFLORA FLOWER; NOTOPTERYGIUM FRANCHETII ROOT; PLANTAGO SEED; SAPOSHNIKOVIA DIVARICATA ROOT; XANTHIUM; CELLULOSE, MICROCRYSTALLINE; POWDERED CELLULOSE; LIGUSTICUM SINENSE ROOT    

Sinus Clear

ACTIVE INGREDIENT

ACTIVE INGREDIENTS: Hepar sulphuris calcareum 10X, Kali bichromicum 10X, Pulsatilla 10X, Silicea 10X.

PURPOSE

SINUS CLEAR is a carefully formulated homeopathic remedy which effectively relieves nasal congestion and restores free breathing through the nose. Sinus Clear is non-drowsy and produces no side effects.

WARNINGS

WARNINGS: If symptoms do not improve or are accompanied by a fever, consult a doctor. If you are pregnant or nursing a baby, seek the advice of a health care professional before using this product.

Keep this and all other medicines out of the reach of children.
Do not use if tamper resistant seal is broken.

DOSAGE AND ADMINISTRATION

DIRECTIONS: Adults and children 12 and over take 1 capsule 3 times daily before meals.

INACTIVE INGREDIENT

OTHER INGREDIENTS: Chinese cimicifuga root, Chinese locorice root, Chinese lovage root, cnidium root, Fragrant angelica root, Green tea leaf, Magnolia flower, Notopterygium root, Psyllium seed, Siler root, Xanthium fruit, Microcrystalline cellulose, Cellulose capsule.

KEEP OUT OF REACH OF CHILDREN

KEEP THIS AND ALL OTHER MEDICINES OUT OF THE REACH OF CHILDREN.

INDICATIONS AND USAGE

SINUS CLEAR is a carefully formulated homeopathic remedy which effectively relieves nasal congestion and restores free breathing through the nose. Sinus Clear is non-drowsy and produces no side effects.

QUESTIONS

Manufactured for:

RidgeCrest Herbals, Inc.

3683 West 2270 South, Ste A

Salt Lake City, UT 84120-2306

phone: 1-800-242-4649

www.ridgecrestherbals.com

PACKAGE LABEL

RIDGECREST HERBALS

Sinus Clear

Homeopathic/Herbal Nasal Decongestant

30 Capsules